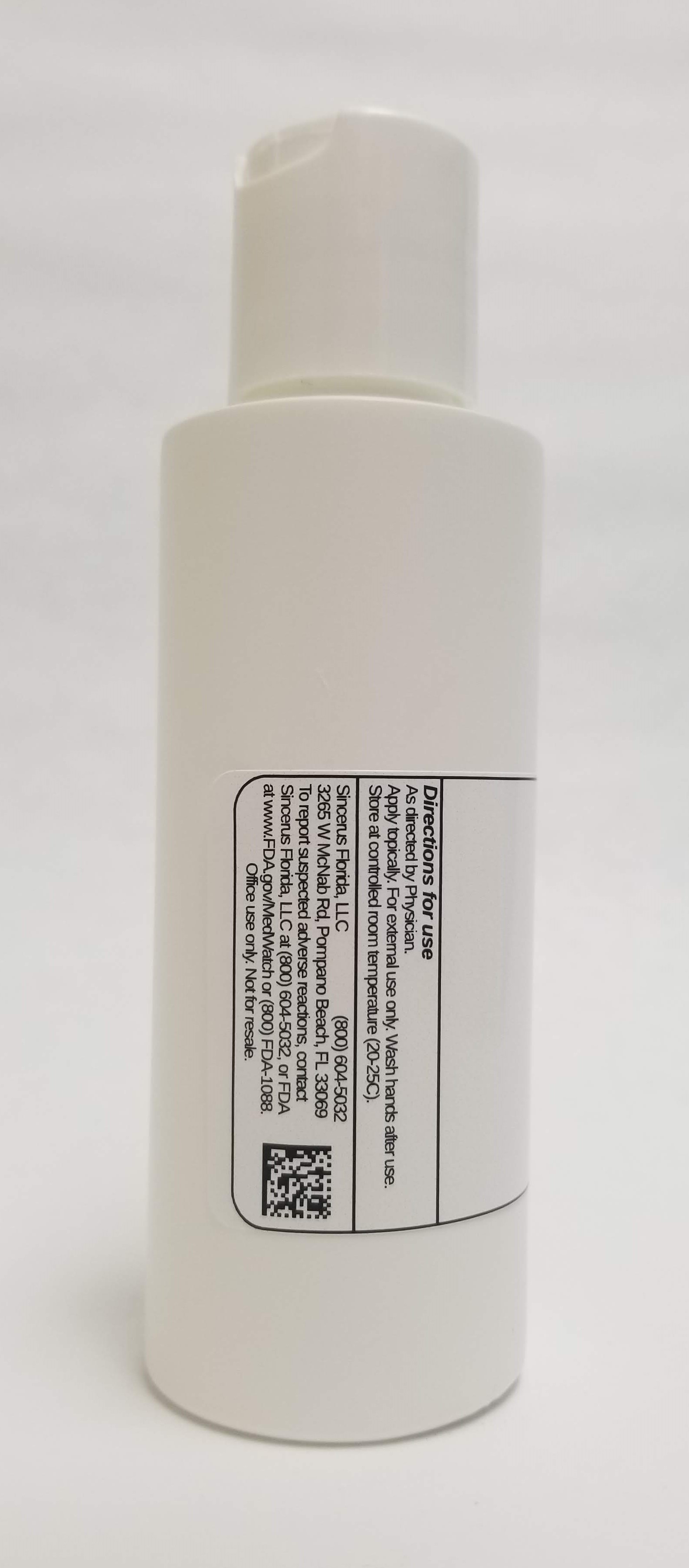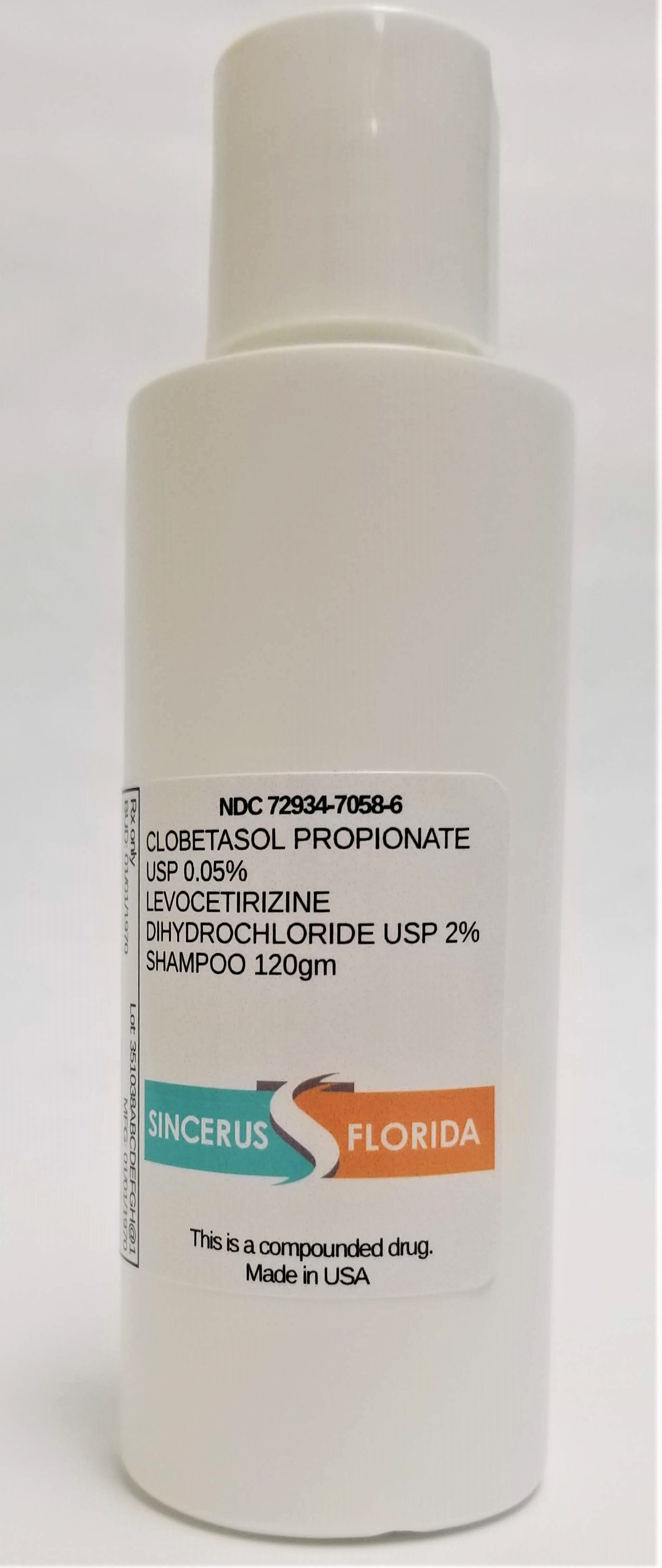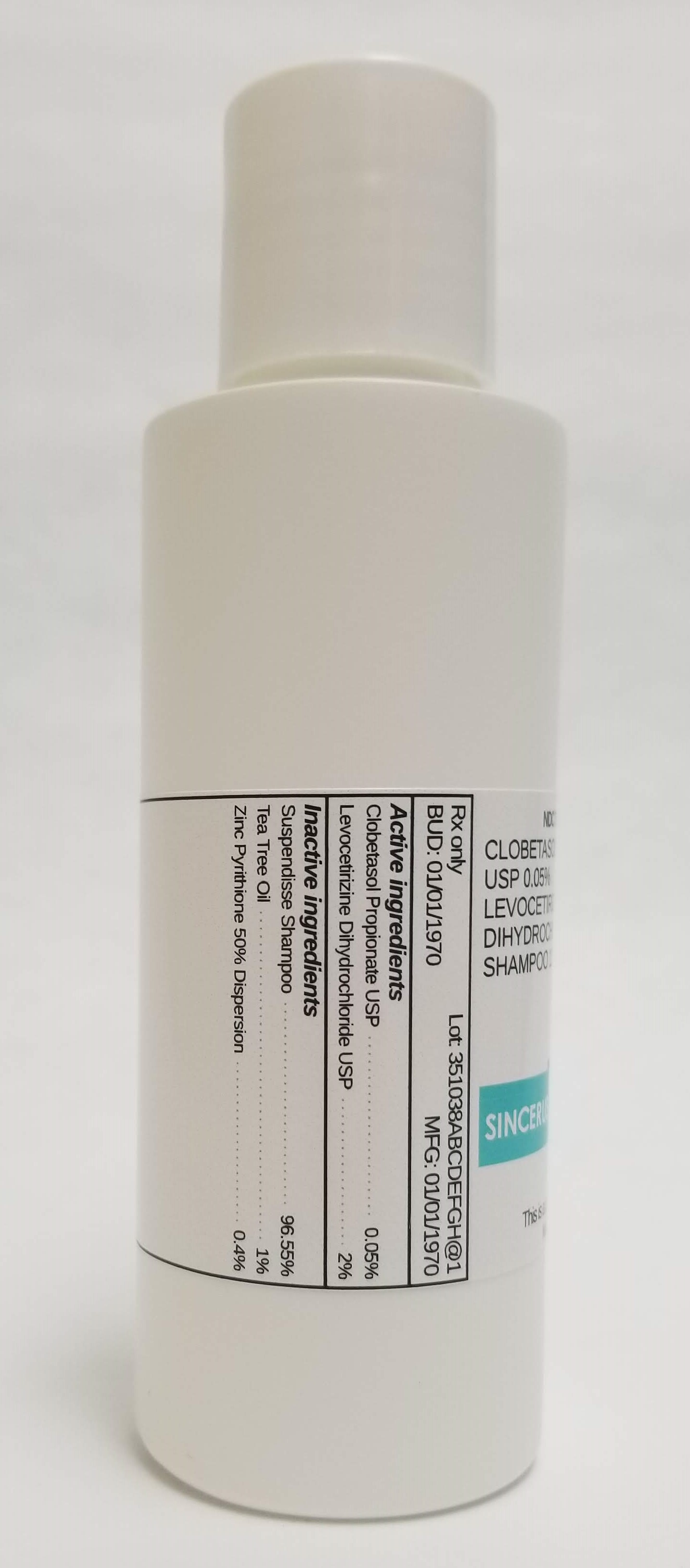 DRUG LABEL: CLOBETASOL PROPIONATE 0.05% / LEVOCETIRIZINE DIHYDROCHLORIDE 2%
NDC: 72934-7058 | Form: SHAMPOO
Manufacturer: Sincerus Florida, LLC
Category: prescription | Type: HUMAN PRESCRIPTION DRUG LABEL
Date: 20190516

ACTIVE INGREDIENTS: CLOBETASOL PROPIONATE 0.05 g/100 g; LEVOCETIRIZINE DIHYDROCHLORIDE 2 g/100 g

CLOBETASOL PROPIONATE 0.05% / LEVOCETIRIZINE DIHYDROCHLORIDE 2%